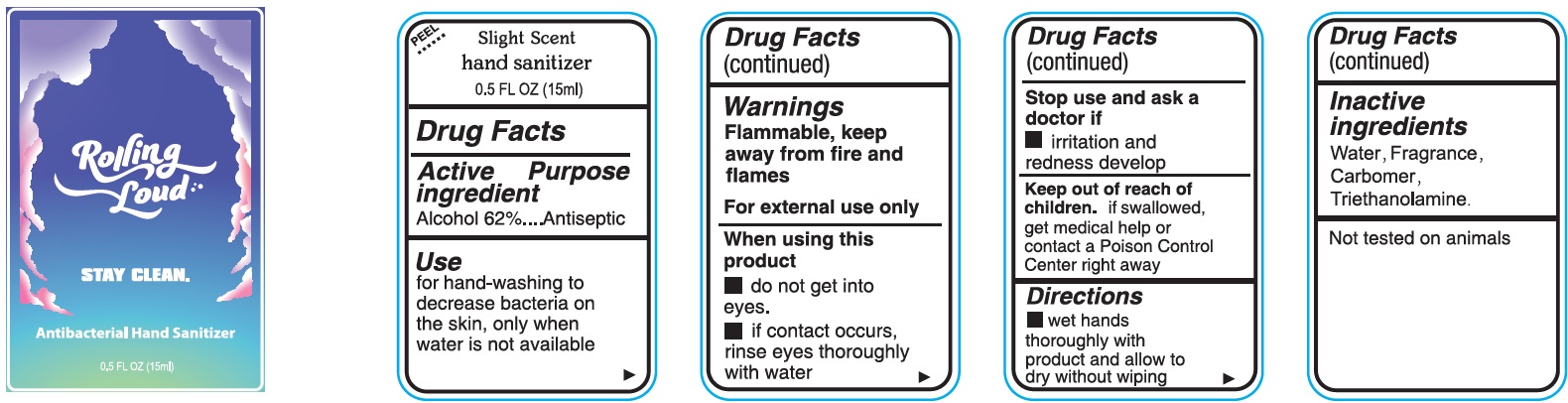 DRUG LABEL: Slight Scent Hand Sanitizer
NDC: 74641-000 | Form: GEL
Manufacturer: Sobe Promos LLC
Category: otc | Type: HUMAN OTC DRUG LABEL
Date: 20231025

ACTIVE INGREDIENTS: ALCOHOL 0.62 mL/1 mL
INACTIVE INGREDIENTS: WATER; CARBOMER HOMOPOLYMER, UNSPECIFIED TYPE; TROLAMINE

Slight Scent Hand Sanitizer

Active ingredient

Alcohol 62%

Purpose

Antiseptic

Use

for hand-washing to decrease bacteria on the skin, only when water is not available

Warnings

Flammable, keep away from fire and flames

For external use only

When using this product

- do not get into eyes.
- if contact occurs, rinse eyes thoroughly with water

Stop use and ask a doctor if

- irritation and redness develop

Keep out of reach of children.

if swallowed, get medical help or contact a Poison Control Center right away

Directions

- wet hands thoroughly with product and allow to dry without wiping

Inactive ingredients

Water, Fragrance, Carbomer, Triethanolamine.

Not tested on animals